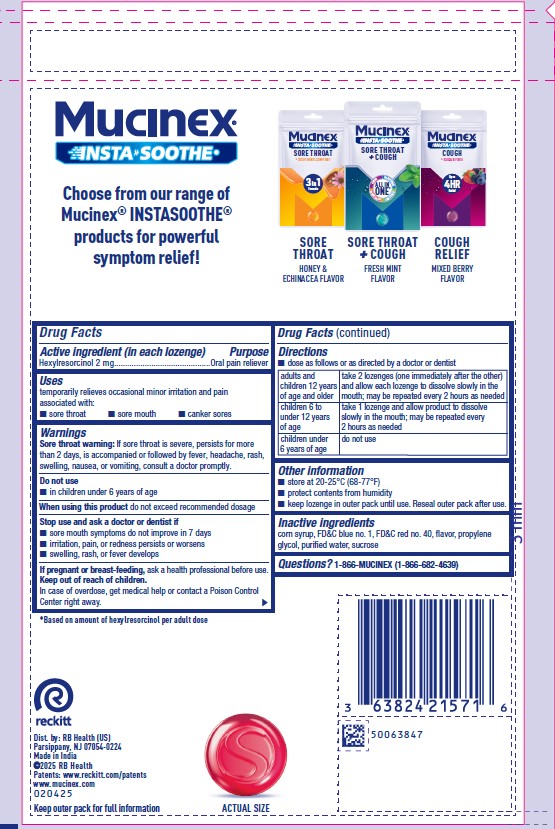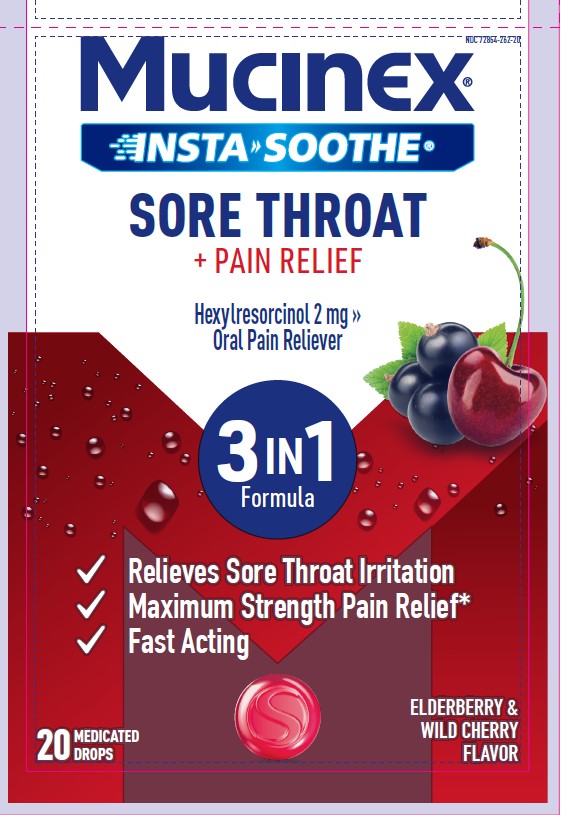 DRUG LABEL: MUCINEX INSTASOOTHE
NDC: 72854-262 | Form: LOZENGE
Manufacturer: RB Health (US) LLC
Category: otc | Type: HUMAN OTC DRUG LABEL
Date: 20251105

ACTIVE INGREDIENTS: HEXYLRESORCINOL 2 mg/1 1
INACTIVE INGREDIENTS: CORN SYRUP; FD&C BLUE NO. 1; FD&C RED NO. 40; PROPYLENE GLYCOL; SUCROSE; WATER

MUCINEX® INSTASOOTHE™
SORE THROAT PLUS PAIN RELIEF

Drug Facts

Active ingredient (in each lozenge)

Hexylresorcinol 2 mg

Purpose

Oral pain reliever

Uses

temporarily relieves occasional minor irritation and pain associated with

- sore throat
- sore mouth
- canker sores

Warnings

Sore throat warning

If sore throat is severe, persists for more than 2 days, is accompanied or followed by fever, headache, rash, swelling, nausea, or vomiting, consult a doctor promptly.

Do not use

- in children under 6 years of age

When using this productdo not exceed recommended dosage

Stop use and ask a doctor or dentist if

- sore mouth symptoms do not improve in 7 days
- irritation, pain, or redness persists or worsens
- swelling, rash, or fever develops

PREGNANCY OR BREAST FEEDING

If pregnant or breast-feeding,ask a health professional before use.

Keep out of reach of children.In case of overdose, get medical help or contact a Poison Control Center right away.

Directions

- dose as follows or as directed by a doctor or dentist

adults and children 12 years of age and older | take 2 lozenges (one immediately after the other) and allow each lozenge to dissolve slowly in the mouth; may be repeated every 2 hours as needed
children 6 to under 12 years of age | take 1 lozenge and allow product to dissolve slowly in the mouth; may be repeated every 2 hours as needed
children under 6 years of age | do not use

Other information

- store at 20-25°C (68-77°F)
- protect contents from humidity
- keep lozenge in outer pack until use. Reseal outer pack after use.

Inactive ingredients

corn syrup, FD&C blue no. 1, FD&C red no. 40, flavor, propylene glycol, purified water, sucrose

Questions?

1-866-MUCINEX (1-866-682-4639)

Dist. By: RB Health (US)
Parsippany, NJ 07054-0224

Made in India

PRINCIPAL DISPLAY PANEL - 20 Drop Pouch Bag

NDC 72854-262-20

Mucinex®

INSTA>>SOOTHE®

SORE THROAT
+ PAIN RELIEF

Hexylresorcinol 2 mg >> Oral Pain Reliever

3 IN 1 FORMULA

✓ Relieves Sore Throat Irritation

✓ Maximum Strength Pain Relief*

✓ Fast Acting

ELDERBERRY &
WILD CHERRY FLAVOR

20 CT MEDICATED DROPS